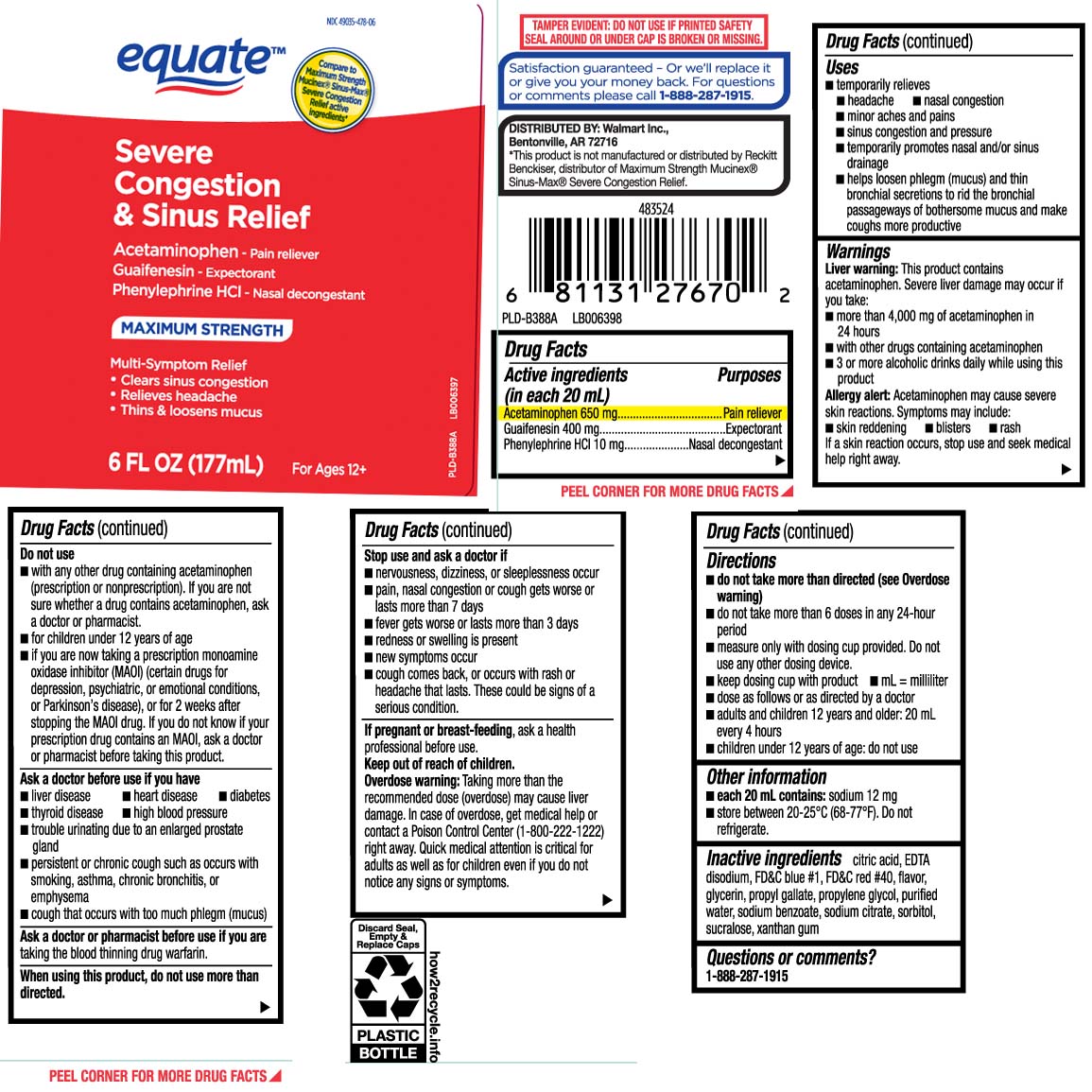 DRUG LABEL: Severe Congestion and Sinus Relief
NDC: 49035-478 | Form: LIQUID
Manufacturer: EQUATE (Wal-Mart Stores, Inc.) (see also WAL-MART INC)
Category: otc | Type: HUMAN OTC DRUG LABEL
Date: 20240322

ACTIVE INGREDIENTS: ACETAMINOPHEN 650 mg/20 mL; GUAIFENESIN 400 mg/20 mL; PHENYLEPHRINE HYDROCHLORIDE 10 mg/20 mL
INACTIVE INGREDIENTS: ANHYDROUS CITRIC ACID; EDETATE DISODIUM; FD&C BLUE NO. 1; FD&C RED NO. 40; GLYCERIN; PROPYL GALLATE; PROPYLENE GLYCOL; WATER; SODIUM BENZOATE; TRISODIUM CITRATE DIHYDRATE; SORBITOL; SUCRALOSE; XANTHAN GUM

Drug Facts

Active ingredients (in each 20 mL)

Acetaminophen 650 mg

Guaifenesin 400 mg

Phenylephrine HCl 10 mg

Purposes

Pain reliever

Expectorant

Nasal decongestant

Uses

- temporarily relieves
  - headache
  - nasal congestion
  - minor aches and pains
  - sinus congestion and pressure
  - temporarily promotes nasal and/or sinus drainage
  - helps loosen phlegm (mucus) and thin bronchial secretions to rid the bronchial passageways of bothersome mucus and make coughs more productive

Warnings

Liver warning: This product contains acetaminophen. Severe liver damage may occur if you take:

- more than 4,000 mg of acetaminophen in 24 hours
- with other drugs containing acetaminophen
- 3 or more alcoholic drinks daily while using this product

Allergy alert: Acetaminophen may cause severe skin reactions. Symptoms may include:

- skin reddening
- blisters
- rash

If a skin reaction occurs, stop use and seek medical help right away.

Do not use

- with any other drug containing acetaminophen (prescription or nonprescription). If you are not sure whether a drug contains acetaminophen, ask a doctor or pharmacist.
- for children under 12 years of age
- if you are now taking a prescription monoamine oxidase inhibitor (MAOI) (certain drugs for depression, psychiatric or emotional conditions, or Parkinson's disease), or for 2 weeks after stopping the MAOI drug. If you do not know if your prescription drug contains an MAOI, ask a doctor or pharmacist before taking this product.

Ask a doctor before use if you have

- liver disease
- heart disease
- diabetes
- thyroid disease
- high blood pressure
- trouble urinating due to an enlarged prostate gland
- persistent or chronic cough such as occurs with smoking, asthma, chronic bronchitis, or emphysema
- cough that occur with too much phlegm (mucus)

Ask a doctor or pharmacist before use if you are

taking the blood thinning drug warfarin.

When using this product,

do not use more than directed.

Stop use and ask a doctor if

- nervousness, dizziness,or sleeplessness occur
- pain, nasal congestion or cough gets worse or lasts more than 7 days
- fever gets worse or last more than 3 days
- redness or swelling is present
- new symptoms occur
- cough comes back, or occurs with rash or headache that lasts. These could be signs of a serious condition.

If pregnant or breast-feeding,

ask a health professional before use.

Keep out of reach of children.

Overdose warning: Taking more than the recommended dose (overdose) may cause liver damage. In case of overdose, get medical help or contact a Poison Control Center (1-800-222-1222) right away. Quick medical attention is critical for adults as well as for children even if you do not notice any signs or symptoms.

Directions

- do not take more than directed (see Overdose warning)
- do not take more than 6 doses in any 24-hour period
- measure only with dosing cup provided. Do not use any other dosing device.
- keep dosing cup with product
- mL=milliliter
- dose as follows or as directed by a doctor
- adults and children 12 years and older: 20 mL every 4 hours
- children under 12 years of age: do not use

Other information

- each 20 mL contains: sodium 12 mg
- store between 20-25ºC (68-77ºF). Do not refrigerate.

Inactive ingredients

anhydrous citric acid, EDTA disodium, FD&C blue #1, FD&C red #40, flavor, glycerin, propyl gallate, propylene glycol, purified water, sodium benzoate, sorbitol, sucralose, trisodium citrate dihydrate, xanthan gum

Questions or comments?

Call 1-888-287-1915

Principal Display Panel

Compare to Maximum Strength Mucinex® Sinus-Max® Severe Congestion Relief active ingredients*

Severe Congestion & Sinus Relief

Acetaminophen - Pain Reliever

Guaifenesin - Expectorant

Phenylephrine HCI - Nasal Decongestant

MAXIMUM STRENGTH

Multi-Symptom Relief

- Clear sinus congestion
- Relieves headache
- Thins & loosens mucus

For Ages 12+

FL OZ (mL)

*This product is not manufactured or distributed by Reckitt Benckiser, distributor of Maximum Strength Mucinex® Sinus-Max® Severe Congestion Relief.

TAMPER EVIDENT: DO NOT USE IF PRINTED SAFETY SEAL AROUND OR UNDER CAP IS BROKEN OR MISSING.

DISTRIBUTED BY: Walmart Inc.,

Bentonville, AR 72716

Package Label

EQUATE Severe Congestion & Sinus Relief